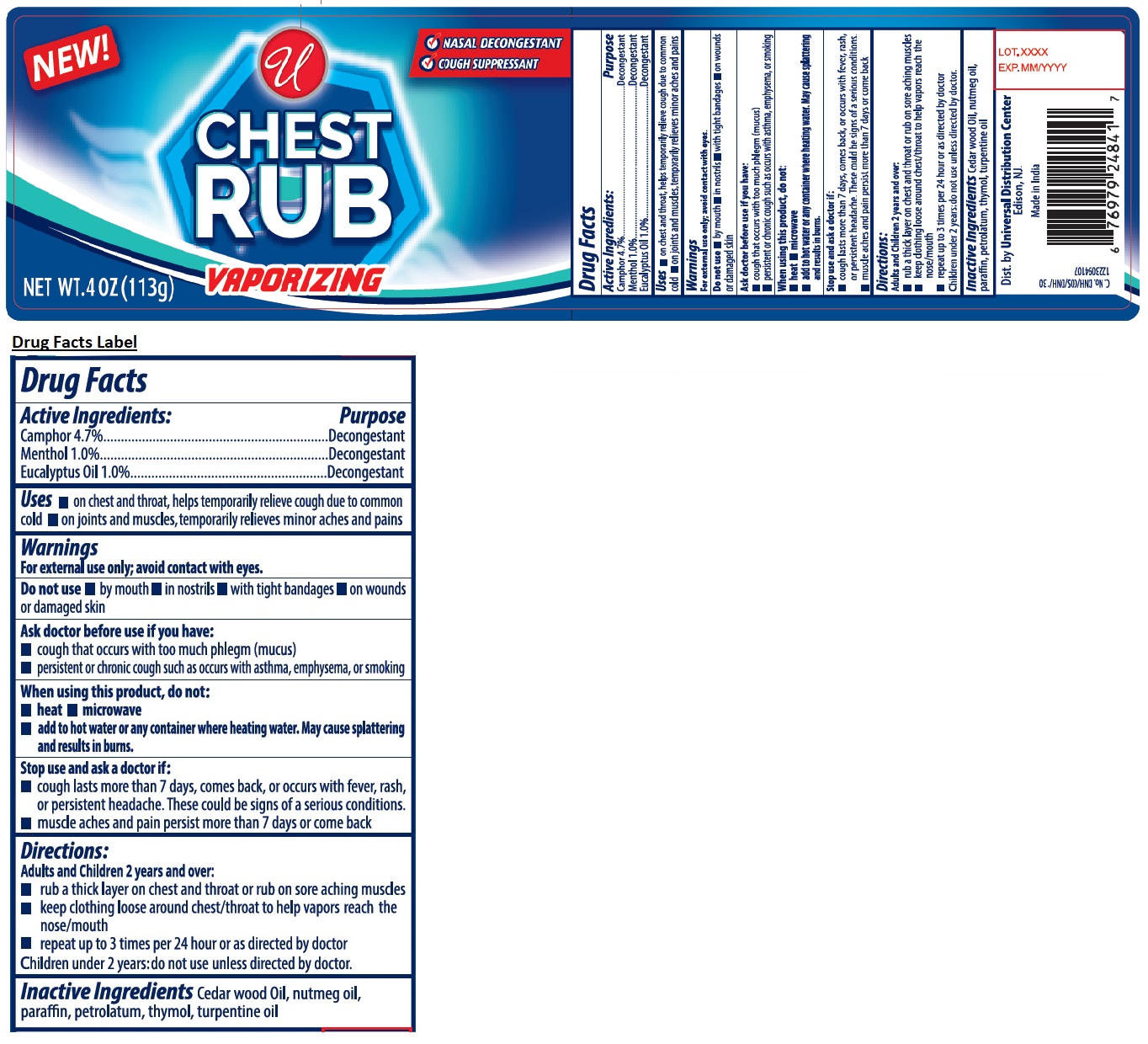 DRUG LABEL: Vaporizing Chest Rub
NDC: 52000-012 | Form: GEL
Manufacturer: Universal Distribution Center LLC
Category: otc | Type: HUMAN OTC DRUG LABEL
Date: 20251027

ACTIVE INGREDIENTS: CAMPHOR (SYNTHETIC) 4.7 g/100 g; MENTHOL, UNSPECIFIED FORM 1 g/100 g; EUCALYPTUS OIL 1 g/100 g
INACTIVE INGREDIENTS: JUNIPERUS VIRGINIANA OIL; NUTMEG OIL; PARAFFIN; PETROLATUM; THYMOL; TURPENTINE OIL

CHEST RUB VAPORIZING

Active Ingredients:

Camphor 4.7%
Menthol 1.0%
Eucalyptus Oil 1.0%

Purpose

Decongestant

Uses

• on chest and throat, helps temporarily relive cough due to common cold • on joints and muscles, temporarily relives minor aches and pains

Warnings

For external use only; avoid contact with eyes.

Do not use • by mouth • in nostrils • with tight bandages • on wounds or damaged skin

Ask doctor before use if you have:
• cough that occurs with too much phlegm (mucus)
• persistent or chronic cough such as occurs with asthma, emphysema, or smoking

When using this product, do not:
• heat • microwave
• add to hot water or any container where heating water. May cause splattering and results in burns.

Stop use and ask a doctor if:
• cough lasts more than 7 days, comes back, or occurs with fever, rash, or persistent headache. These could be signs of a serious conditions.
• muscle aches or pain persist more than 7 days or come back

Keep out of the reach of children
If ingested get medical help or contact a Poison control center immediately

Directions:

Adults and children 2 years and over:
• rub a thick layer on chest and throat or rub on sore aching muscles
• keep clothing loose around chest/throat to help vapors reach the nose/mouth
• repeat up to 3 times per 24 hour or as directed by doctor
Children under 2 years: do not use unless directed by doctor.

Inactive Ingredients

Cedar wood Oil, nutmeg oil, paraffin, petrolatum, thymol, turpentine oil

NEW!

NASAL DECONGESTANT

COUGH SUPPRESSANT

Dist. by Universal Distribution Center
Edison, NJ.

Made in India